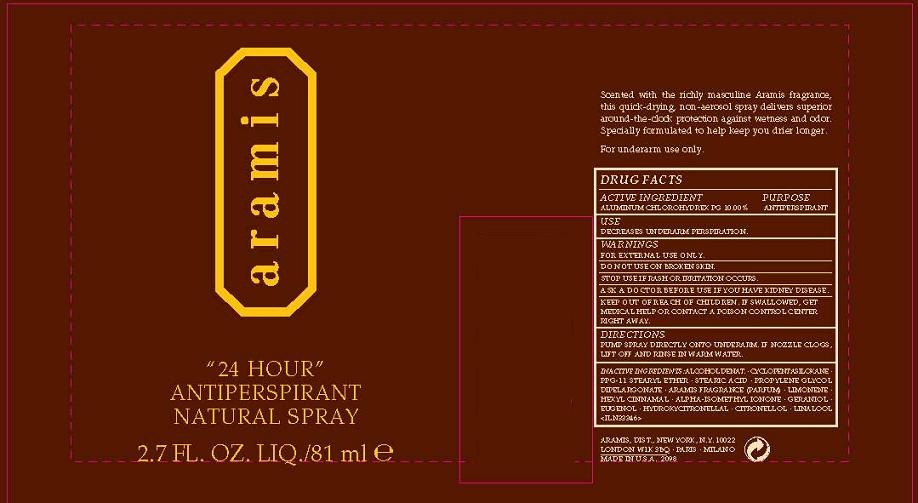 DRUG LABEL: 24 HOUR 
NDC: 42472-001 | Form: SPRAY
Manufacturer: ARAMIS INC.
Category: otc | Type: HUMAN OTC DRUG LABEL
Date: 20110805

ACTIVE INGREDIENTS: ALUMINUM CHLOROHYDREX PROPYLENE GLYCOL 10 mL/100 mL
INACTIVE INGREDIENTS: ALCOHOL; CYCLOMETHICONE 5; STEARIC ACID; PROPYLENE GLYCOL DIETHYLHEXANOATE

ACTIVE INGREDIENT: ALUMINUM CHLOROHYDREX PG 10.00%

INACTIVE INGREDIENT

INACTIVE INGREDIENTS: ALCOHOL DENAT. [] CYCLOPENTASILOXANE [] PPG-11 STEARYL ETHER [] STEARIC ACID [] PROPYLENE GLYCOL DIPELARGONATE [] ARAMIS FRAGRANCE (PARFUM) [] LIMONENE [] HEXYL CINNAMAL [] ALPHA-ISOMETHYL IONONE [] GERANIOL [] EUGENOL [] HYDROXYCITRONELLAL [] CITRONELLOL [] LINALOOL

PURPOSE: ANTIPERSPIRANT

INDICATIONS AND USAGE

USE: REDUCES UNDERARM WETNESS

WARNINGS:

- FOR EXTERNAL USE ONLY
- DO NOT USE ON BROKEN SKIN
- STOP USE IF IRRITATION OCCURS

ASK A DOCTOR BEFORE USE IF YOU HAVE KIDNEY DISEASE.

KEEP OUT OF REACH OF CHILDREN. IF SWALLOWED, GET MEDICAL HELP OR CONTACT A POISON CONTROL CENTER IMMEDIATELY.

DOSAGE AND ADMINISTRATION

DIRECTIONS: PUMP SPRAY DIRECTLY ONTO UNDERARM. IF NOZZLE CLOGS, LIFT OFF AND RINSE IN WARM WATER.

PACKAGE LABEL

PRINCIPAL DISPLAY PANEL:

ARAMIS

24 HOUR

ANTIPERSPIRANT
NATURAL SPRAY

NT WT 2.7 OZ/ 81 ML

ARAMIS DISTR,

NY, NY 10022